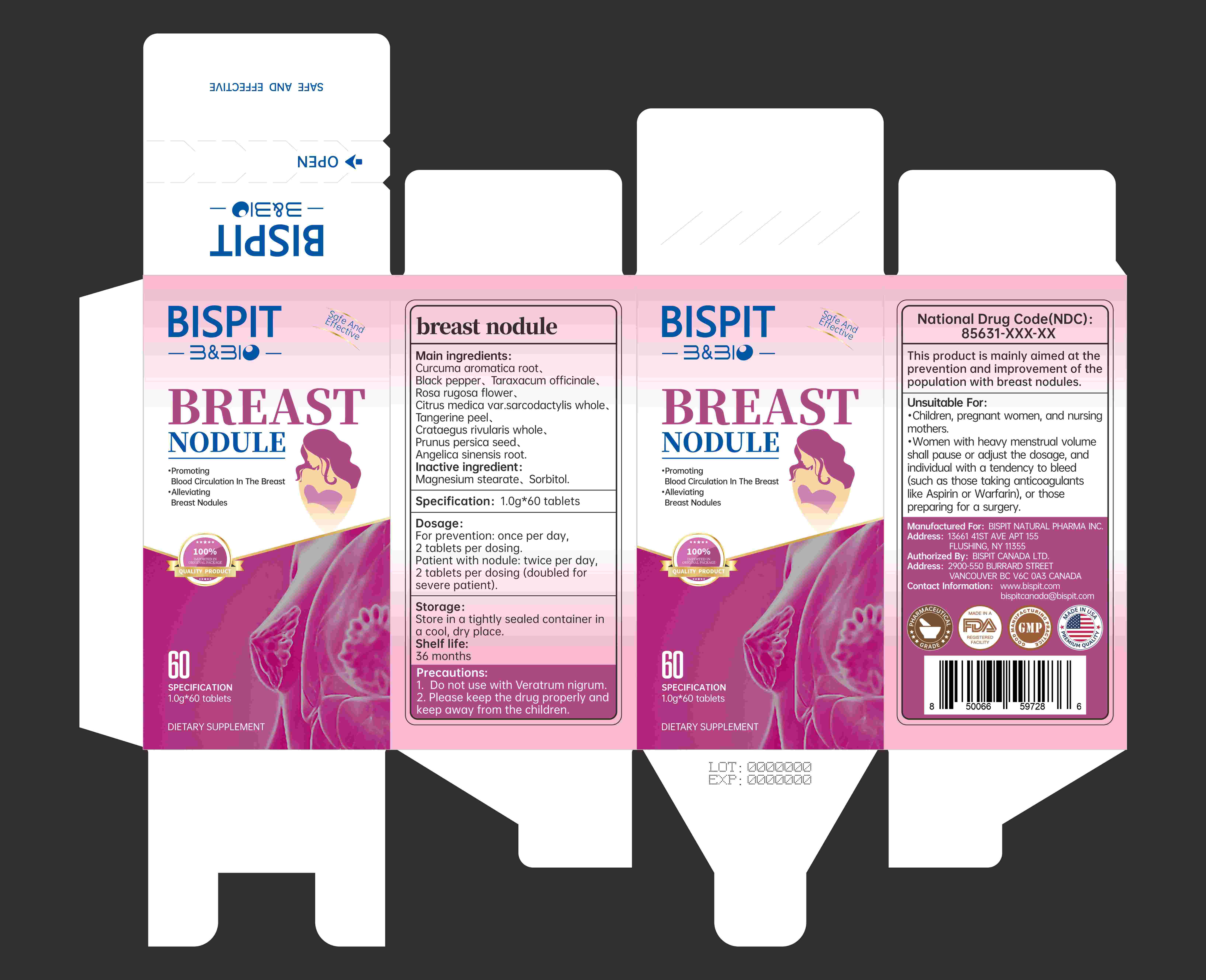 DRUG LABEL: BREAST NODULE
NDC: 85631-010 | Form: CAPSULE
Manufacturer: Bispit Canada Ltd.
Category: homeopathic | Type: HUMAN OTC DRUG LABEL
Date: 20251103

ACTIVE INGREDIENTS: CITRUS MEDICA VAR. SARCODACTYLIS WHOLE 30 mg/1 g; BLACK PEPPER 2 mg/1 g; ROSA RUGOSA FLOWER 70 mg/1 g; PRUNUS PERSICA SEED 30 mg/1 g; TANGERINE PEEL 30 mg/1 g; CRATAEGUS RIVULARIS WHOLE 30 mg/1 g; TARAXACUM OFFICINALE 90 mg/1 g; CURCUMA AROMATICA ROOT 510 mg/1 g; ANGELICA SINENSIS ROOT 30 mg/1 g
INACTIVE INGREDIENTS: MAGNESIUM STEARATE; SORBITOL

ACTIVE INGREDIENT

CURCUMA AROMATICA ROOT
BLACK PEPPER
TARAXACUM OFFICINALE
ROSA RUGOSA FLOWER
CITRUS MEDICA VAR. SARCODACTYLIS WHOLE
TANGERINE PEEL
CRATAEGUS RIVULARIS WHOLE
PRUNUS PERSICA SEED
ANGELICA SINENSIS ROOT

KEEP OUT OF REACH OF CHILDREN

1. Do not use with Veratrum nigrum.2. Please keep the drug properly andkeep away from the children.

PURPOSE

Promoting

Blood Circulation in The Breast
Alleviating
Breast Nodules

INDICATIONS AND USAGE

Dosage:For prevention: once per day,2 tablets per dosing.Patient with nodule: twice per day.2 tablets per dosing (doubled forsevere patient).

DOSAGE AND ADMINISTRATION

For prevention: once per day,2 tablets per dosing.Patient with nodule: twice per day,2 tablets per dosing (doubled forsevere patient).

WARNINGS

Unsuitable For:*Children, pregnant women, and nursingmothers.
Women with heavy menstrual volumeshall pause or adjust the dosage, andindividual with a tendency to bleed(such as those taking anticoagulantslike Aspirin or Warfarin), or thosepreparing for a surgery.

INACTIVE INGREDIENT

Magnesium stearate、 Sorbitol.